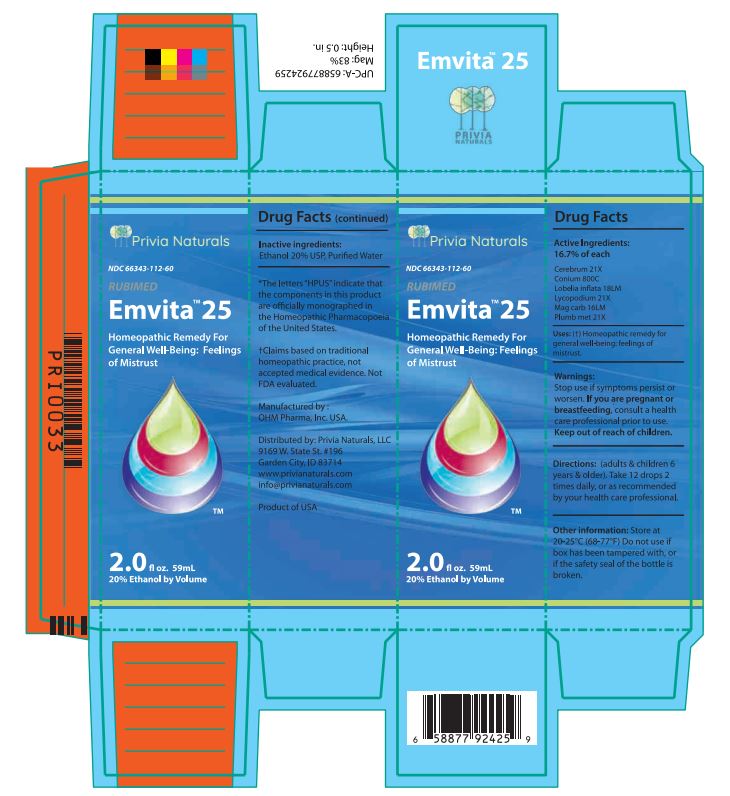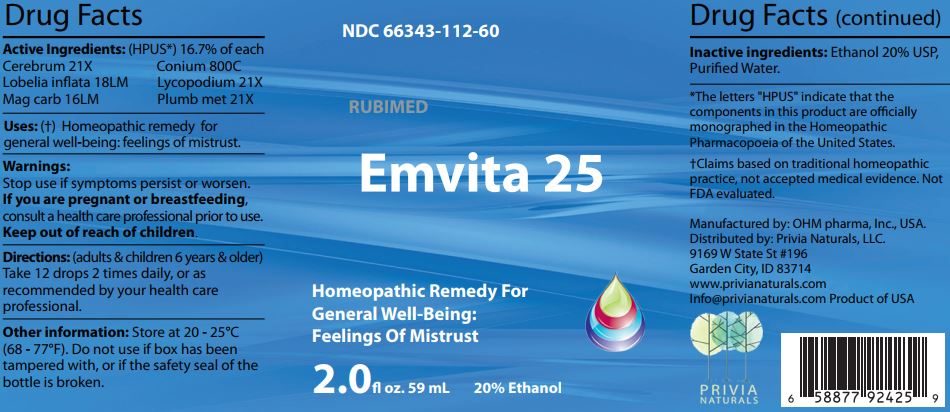 DRUG LABEL: Emvita 25
NDC: 66343-112 | Form: LIQUID
Manufacturer: RUBIMED AG
Category: homeopathic | Type: HUMAN OTC DRUG LABEL
Date: 20241029

ACTIVE INGREDIENTS: SUS SCROFA CEREBRUM 21 [hp_X]/60 mL; CONIUM MACULATUM FLOWERING TOP 800 [hp_C]/60 mL; LOBELIA INFLATA WHOLE 18 [hp_M]/60 mL; LYCOPODIUM CLAVATUM SPORE 21 [hp_X]/60 mL; MAGNESIUM CARBONATE 16 [hp_M]/60 mL; LEAD 21 [hp_X]/60 mL
INACTIVE INGREDIENTS: ALCOHOL; WATER

Emvita 25

ACTIVE INGREDIENT

Drug Facts Active Ingredients: (HPUS*) 16.7% of each

Cerebrum 21X Conium 800C
Lobelia inflata 18LM Lycopodium 21X
Mag carb 16LM Plumb met 21X

*The letters "HPUS" indicate that the components in this product are officially monographed in the Homeopathic Pharmacopoeia of the United States. †Claims based on traditional homeopathic practice, not accepted medical evidence. Not FDA evaluated.

INDICATIONS AND USAGE

Uses: (†) Homeopathic remedy for general well being: feelings of mistrust.

Warnings:

Stop use if symptoms persist or worsen.

If you are pregnant or breastfeeding,consult a healthcare professional prior to use.

Keep out of reach of children.

DOSAGE AND ADMINISTRATION

Directions: (adults & children 6 years & older)

Take 12 drops 2 times daily, or as recommended by your health care professional.

Other information: Store at 20 - 25°C

(68 - 77°F.) Do not use if box has been

tampered with, or if the safety seal of the

bottle is broken.

Inactive ingredients:Ethanol 20% USP,

Purified Water.

QUESTIONS

Manufactured by: OHM pharma, Inc, USA.

Distributed by: Privia Naturals, LLC.

9169 W State St #196

Garden City, ID 83714

www.privianaturals.com

Info@privianaturals.com Product of USA.

PACKAGE LABEL

NDC 66343-112-60

RUBIMED

Emvita 25

Homeopathic Medicine For

General Well-being:

Feelings Of Mistrust

2.0 fl oz. 59mL 20% Ethanol

PURPOSE

Homeopathic Medicine For

General Well-being:

Feelings of Mistrust